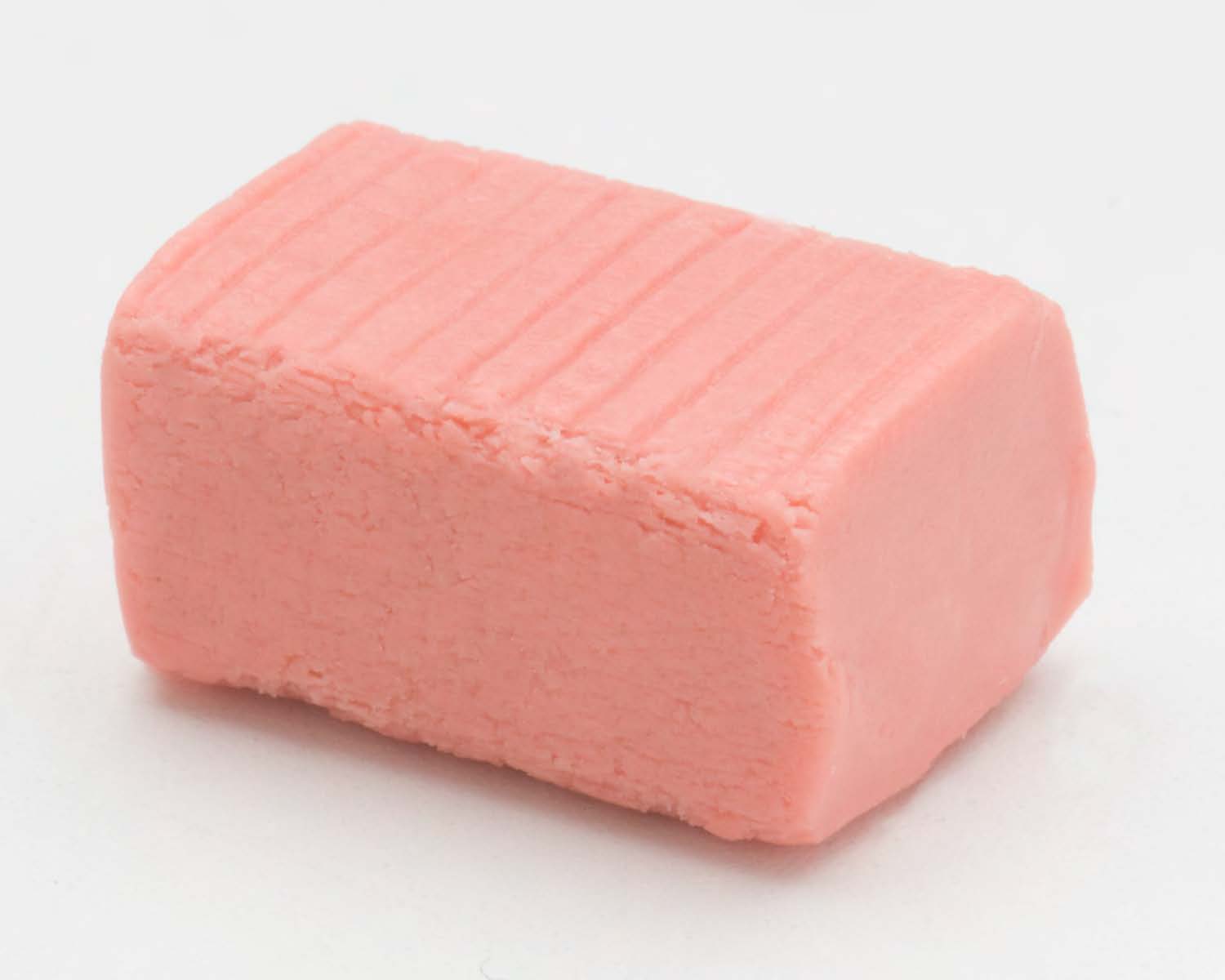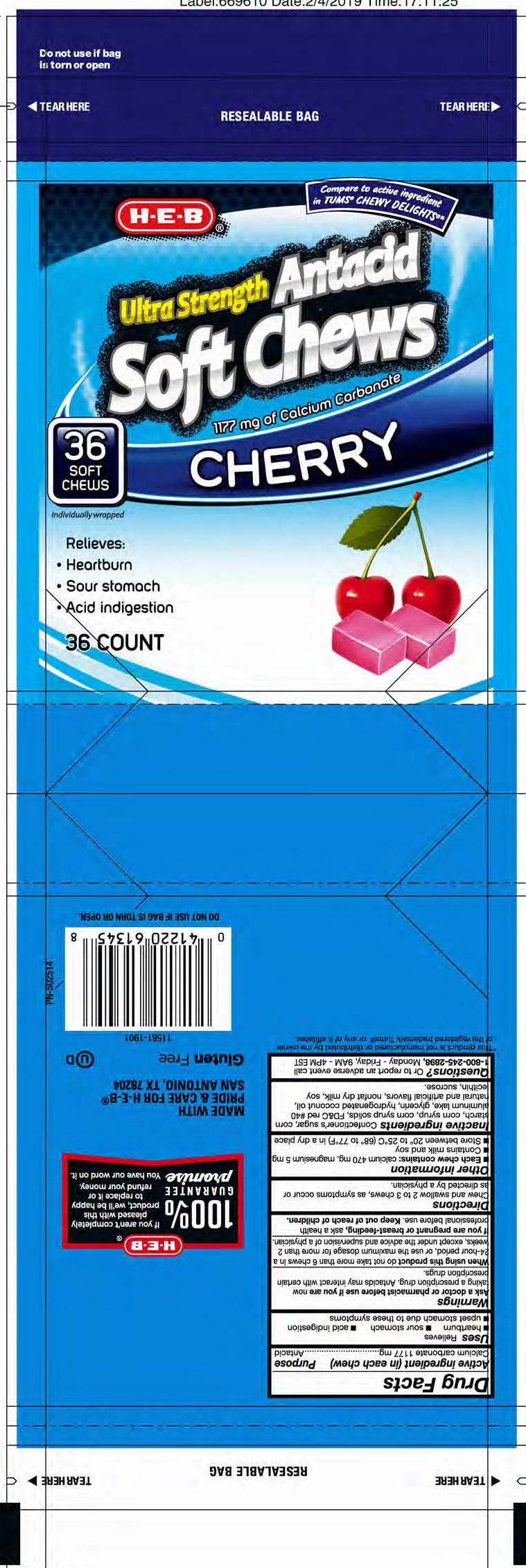 DRUG LABEL: Cherry Antacid Soft Chew
NDC: 37808-058 | Form: TABLET, CHEWABLE
Manufacturer: HEB
Category: otc | Type: HUMAN OTC DRUG LABEL
Date: 20251213

ACTIVE INGREDIENTS: CALCIUM CARBONATE 1177 mg/1 1
INACTIVE INGREDIENTS: WATER

Calcium Carbonate 1177mg

Active ingredient (in each chew)

Calcium carbonate 1177 mg

Purpose

Antacid

INDICATIONS AND USAGE

Uses: Relieves

heartburn sour stomach acid indigestion

upset stomach due to these symptoms

Warnings

Ask a doctor or pharmacist before use if you are now taking a prescription drug. Antacids may interact with certain perscription drugs. Do not take more that 6 hcews in a 24-hour period, or use the maximum dosage for more than 2 weeks, except under the

advice and supervision of a physician.

Keep out of reach of children.

Directions

Chew and swallow 2 to 3 chews, as symptoms occur or as

directed by a physician.

Other information

- Each chew contains: calcium 470 mg, magnesium 5 mg
- Contains milk and soy
- Store between 20° to 25°C (68° to 77°F) in a dry place

Inactive ingredients: corn syrup, corn syrup solids,

FD&C red #40 aluminum lake, glycerin, hydrogenated coconut

oil, natural and artificial flavors, non-fat dairy milk powder, soy

lecithin, sucrose. Soybean oil and corn starch used as

processing aids.

QUESTIONS

Questions? Comments to to report an adverse event call 1-800-245-2898. Monday - Friday, 9AM to 4PM EST